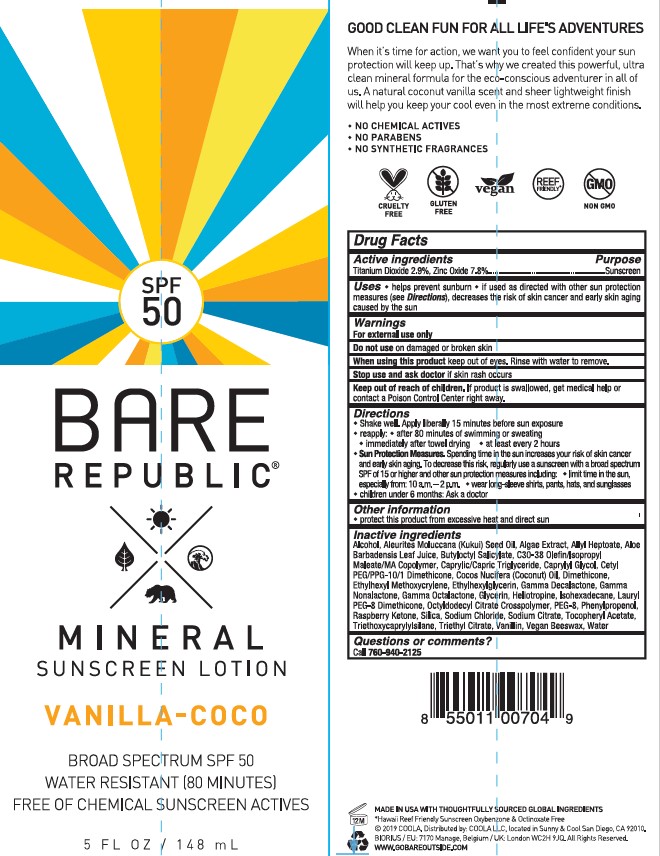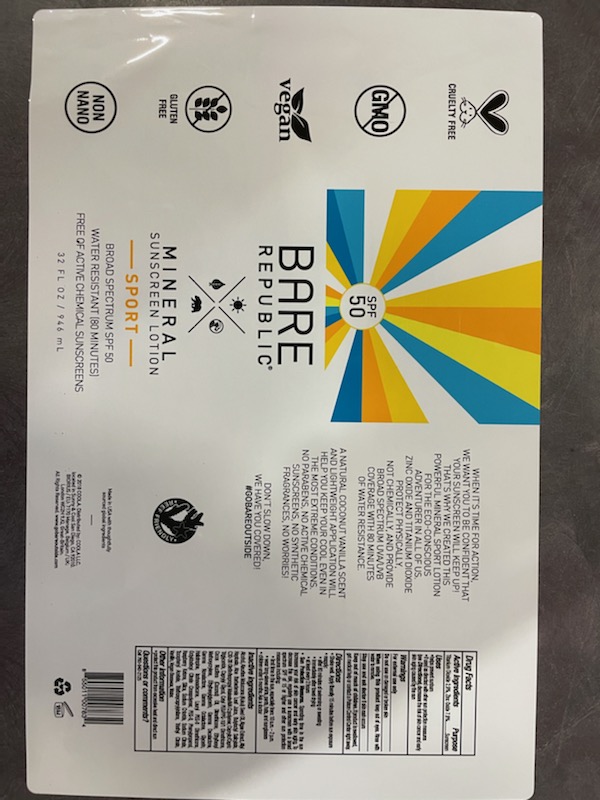 DRUG LABEL: COOLA BARE REPUBLIC MINERAL SPORT SPF50
NDC: 79753-029 | Form: LOTION
Manufacturer: COOLA, LLC
Category: otc | Type: HUMAN OTC DRUG LABEL
Date: 20251214

ACTIVE INGREDIENTS: ZINC OXIDE 78 mg/1 mL; TITANIUM DIOXIDE 29 mg/1 mL
INACTIVE INGREDIENTS: GLYCERIN; KUKUI NUT OIL; ALLYL HEPTANOATE; ISOHEXADECANE; SILICON DIOXIDE; LAURYL PEG/PPG-18/18 METHICONE; BUTYLOCTYL SALICYLATE; CETYL PEG/PPG-10/1 DIMETHICONE (HLB 5); COCONUT OIL; DIMETHICONE; SODIUM CHLORIDE; TRIETHOXYCAPRYLYLSILANE; SYNTHETIC BEESWAX; MEDIUM-CHAIN TRIGLYCERIDES; CAPRYLYL GLYCOL; ETHYLHEXYLGLYCERIN; .GAMMA.-DECALACTONE; .GAMMA.-NONALACTONE; PIPERONAL; OCTYLDODECYL CITRATE CROSSPOLYMER; 3-PHENYL-1-PROPANOL; ALCOHOL; SODIUM CITRATE; .GAMMA.-OCTALACTONE; TRIETHYL CITRATE; PHYMATOLITHON CALCAREUM; ALOE VERA LEAF; ETHYLHEXYL METHOXYCRYLENE; POLYETHYLENE GLYCOL 4000; 4-(P-HYDROXYPHENYL)-2-BUTANONE; .ALPHA.-TOCOPHEROL ACETATE; VANILLIN; WATER

COOLA BARE REPUBLIC MINERAL SPORT SPF50 LOTION

Active ingredients

Titanium Dioxide 2.9%, Zinc Oxide 7.8

Purpose

Sunscreen

Uses

- helps prevent sunburn
- if used as directed with other sun protection measures (see Directions), decreases the risk of skin cancer and early skin aging caused by the sun

Warnings

For external use only

Do not use

- on damaged or broken skin.

When using this product

- keep out of eyes. Rinse with water to remove.

Stop use and ask a doctor if

- rash occurs.

Keep out of the reach of children

If swallowed, get medical help or contact a Poison Control Center right away.

Directions

- apply liberally 15 minutes before sun exposure

- reapply:

-after 80 minutes of swimming or sweating

-immediately after towel drying

-at least every 2 hours

- children under 6 months of age: ask a doctor
- Sun Protection Measures. Spending time in the sun increases your risk of skin cancer and early skin aging. To decrease this risk, regularly use a sunscreen with a Broad Spectrum SPF value of 15 or higher and other sun protection measures including:

-limit time in the sun, especially from 10 a.m.-2 p.m.

-wear long-sleeved shirts, pants, hats, and sunglasses

Other information

- protect this product from excessive heat and direct sun
- may stain or damage some fabrics, materials or surfaces

Inactive Ingredients

Alcohol, AleuritesMoluccana (Kukui) Seed Oil, Algae Exract, Allyl Heptoate, Aloe Barbadensis Leaf Juice, Butyloctyl Salicylate, C30-38 Olefin/Isopropyl Maleate/MA Copolymer, Caprylic/Capric Triglyceride, Caprylyl Glycol, Cetyl PEG/PPG-10/1 Dimethicone, Cocos Nucifera (Coconut) Oil, Dimethicone, Ethylhexyl Methoxycrylene, Ethylhexylglycerin, Gamma Decalactone, Gamma Nonalactone, Gamma Octalactone, Glycerin, Heliotropine, Isohecxadecane, Lauryl PEG-8 Dimethicone, Octyldodecyl Citrate Crosspolymer, PEG-8, Phenylpropenol, Raspberry Ketone, Silica, Sodium Chloride, Sodium Citrate, Tocopheryl Acetate, Triethoxycaprylylsilane, Triethyl Citrate, Vanillin, Vegan Beeswax, Water

Label

res